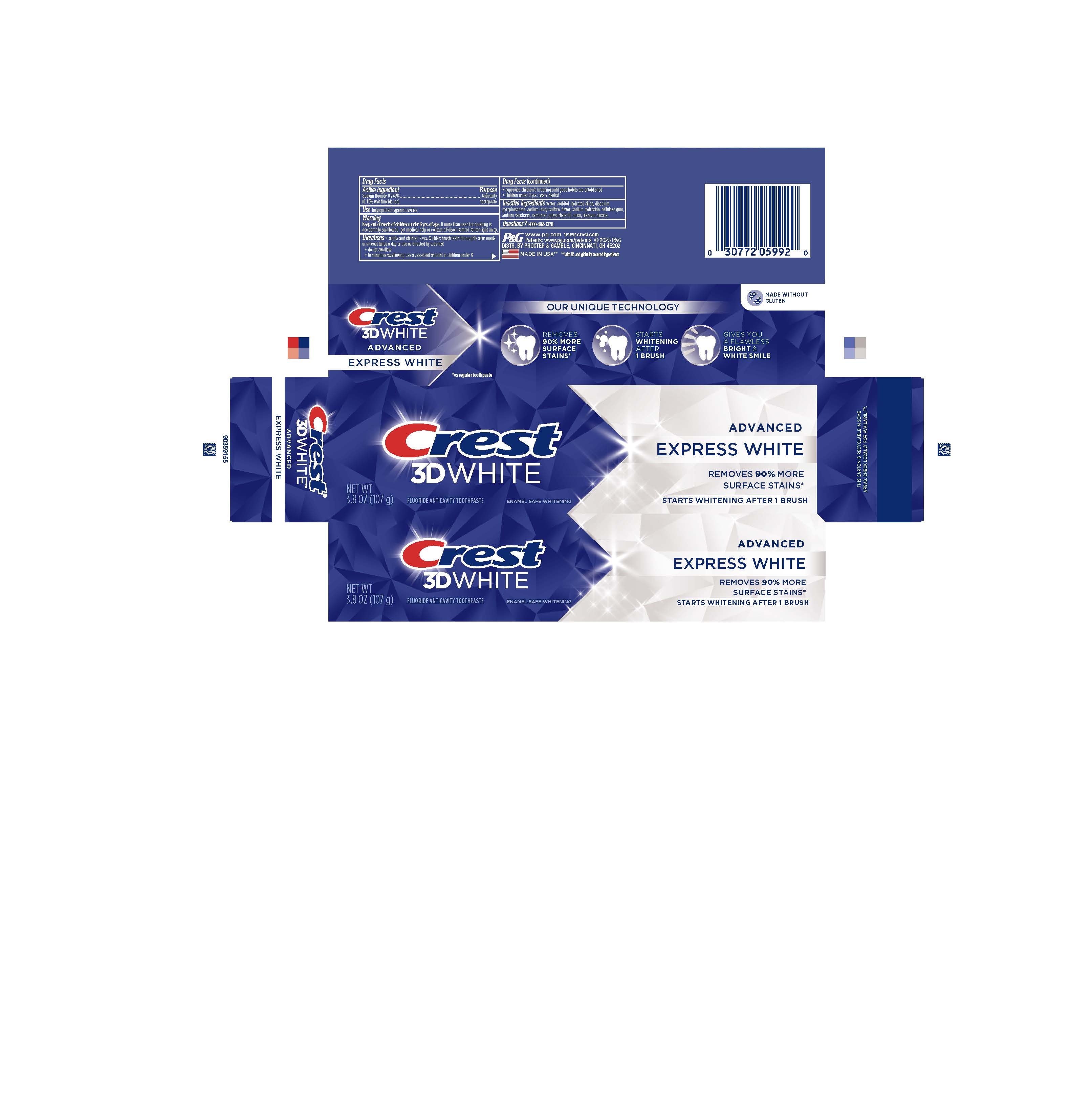 DRUG LABEL: Crest 3D White
NDC: 69423-762 | Form: PASTE, DENTIFRICE
Manufacturer: The Procter & Gamble Manufacturing Company
Category: otc | Type: HUMAN OTC DRUG LABEL
Date: 20260108

ACTIVE INGREDIENTS: SODIUM FLUORIDE 1.5 mg/1 g
INACTIVE INGREDIENTS: SODIUM HYDROXIDE; POLYSORBATE 80; SODIUM ACID PYROPHOSPHATE; SORBITOL; CARBOXYMETHYLCELLULOSE SODIUM; HYDRATED SILICA; WATER; SODIUM LAURYL SULFATE; SACCHARIN SODIUM; MICA; TITANIUM DIOXIDE; CARBOXYPOLYMETHYLENE

Crest 3D White Advanced Express White

Drug Facts

Active ingredient

Sodium fluoride 0.243% (0.15% w/v fluoride ion)

Purpose

Anticavity toothpaste

Use

helps protect against cavities

Warning

Keep out of reach of children under 6 yrs. of age. If more than used for brushing is accidentally swallowed, get medical help or contact a Poison Control Center right away.

Directions

- adults and children 2 yrs. & older: brush teeth thoroughly after meals or at least twice a day or use as directed by a dentist
- do not swallow
- to minimize swallowing use a pea-sized amount in children under 6
- supervise children's brushing until good habits are established
- children under 2 yrs.: ask a dentist

Inactive ingredients

water, sorbitol, hydrated silica, disodium
pyrophosphate, sodium lauryl sulfate, flavor, sodium hydroxide, cellulose gum,
sodium saccharin, carbomer, polysorbate 80, mica, titanium dioxide

Questions?

1-800-492-7378

DISTR. BY PROCTER & GAMBLE, CINCINNATI, OH 45202

PRINCIPAL DISPLAY PANEL - 107 g Tube Carton

Crest
3D White
Advanced
Express White
NET WT 3.8 OZ (107 g)
Fluoride Anticavity Toothpaste
Enamel Safe Whitening
Removes 90% more
Surface Stains*
Starts Whitening After 1 Brush